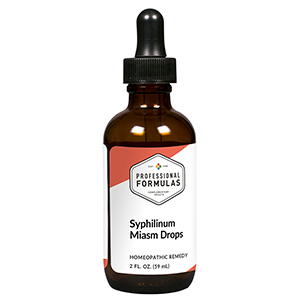 DRUG LABEL: Syphilinum Miasm Drops
NDC: 63083-2064 | Form: LIQUID
Manufacturer: Professional Complementary Health Formulas
Category: homeopathic | Type: HUMAN OTC DRUG LABEL
Date: 20190815

ACTIVE INGREDIENTS: ARSENIC TRIOXIDE 30 [hp_X]/59 mL; FERULA ASSA-FOETIDA RESIN 30 [hp_X]/59 mL; GOLD 30 [hp_X]/59 mL; CARBO ANIMALIS 30 [hp_X]/59 mL; POTASSIUM IODIDE 30 [hp_X]/59 mL; TREPONEMIC SKIN CANKER HUMAN 30 [hp_X]/59 mL; MERCURIC CHLORIDE 30 [hp_X]/59 mL; PENICILLIN G 200 [hp_X]/59 mL
INACTIVE INGREDIENTS: ALCOHOL; WATER

C64

ACTIVE INGREDIENTS

Arsenicum album 30X
Asafoetida 30X
Aurum metallicum 30X
Carbo animalis 30X
Kali iodatum 30X
Syphilinum 30X
Mercurius corrosivus 30X, 200X
Penicillinum 200X

QUESTIONS

Professional Formulas

PO Box 2034 Lake Oswego, OR 97035

INDICATIONS

For the temporary relief of skin or mouth ulcers, minor bone aches or pains, anxiousness, insomnia, or pessimism consistent with classical syphilinum miasm.*

PURPOSE

*Claims based on traditional homeopathic practice, not accepted medical evidence. Not FDA evaluated.

WARNINGS

In case of overdose, get medical help or contact a poison control center right away.

Keep out of the reach of children.

PREGNANCY OR BREAST FEEDING

If pregnant or breastfeeding, ask a healthcare professional before use.

DIRECTIONS

Place drops under tongue 30 minutes before/after meals. Adults and children 12 years and over: Take 10 drops up to 3 times per day. Consult a physician for use in children under 12 years of age.

OTHER INFORMATION

Tamper resistant. If seal is broken, do not use. After opening, close container tightly and store at room temperature away from heat.

INACTIVE INGREDIENTS

20% ethanol, purified water.

LABEL

Est 1985

Professional Formulas

Complementary Health

Syphilinum Miasm Drops

Homeopathic Remedy

2 FL. OZ. (59 mL)